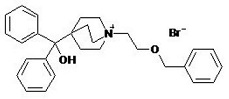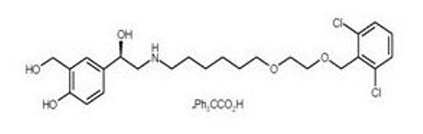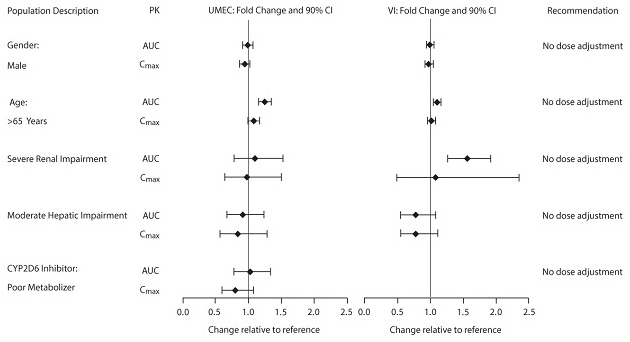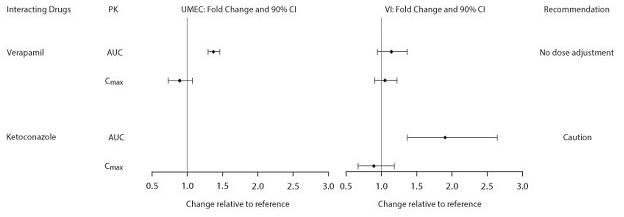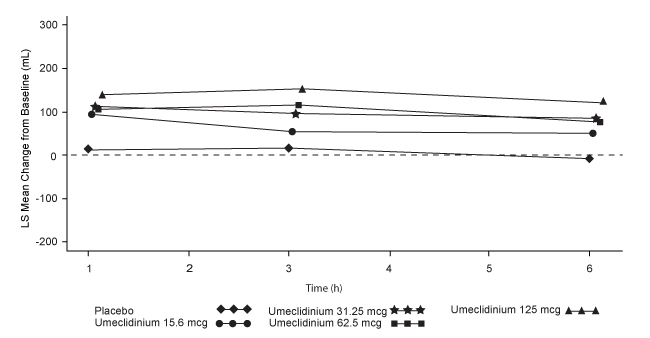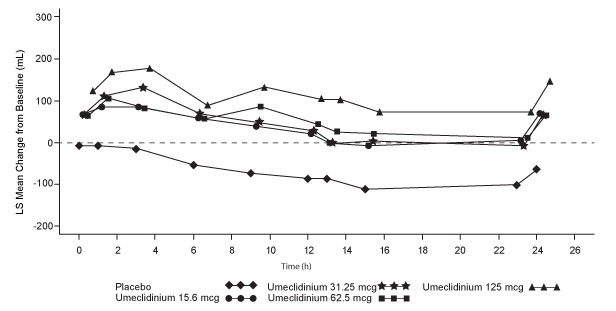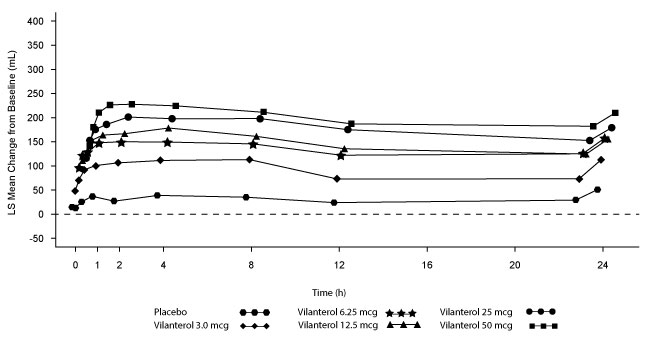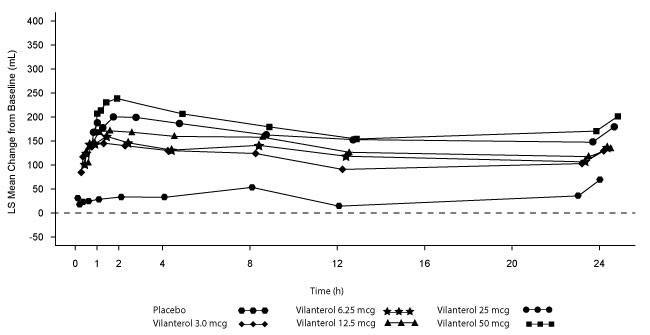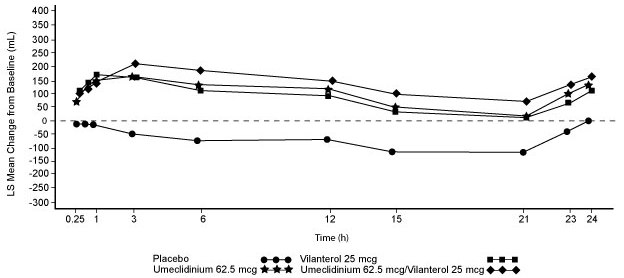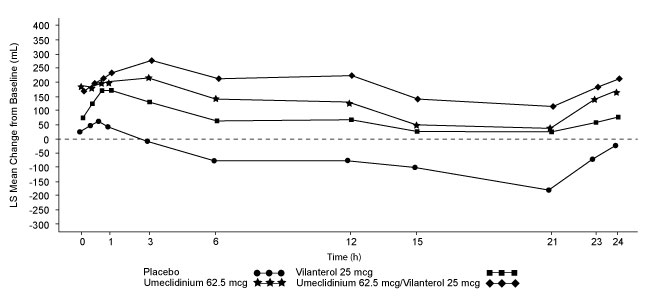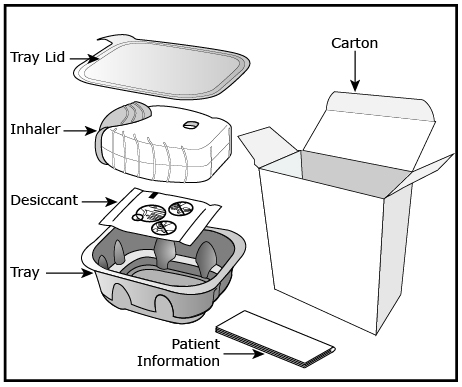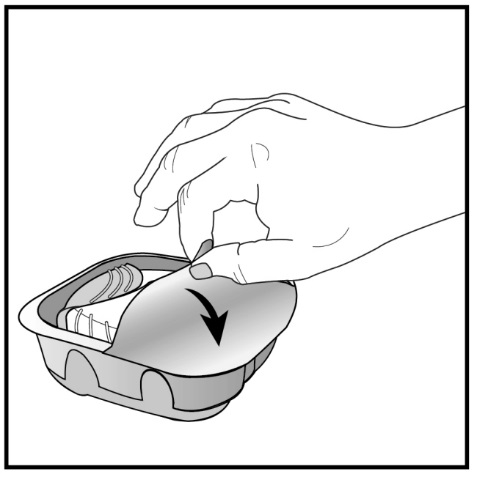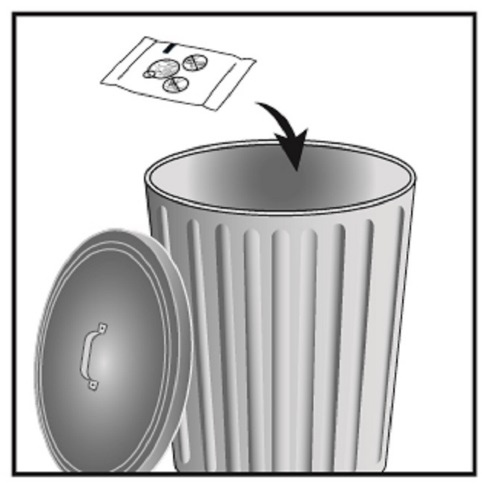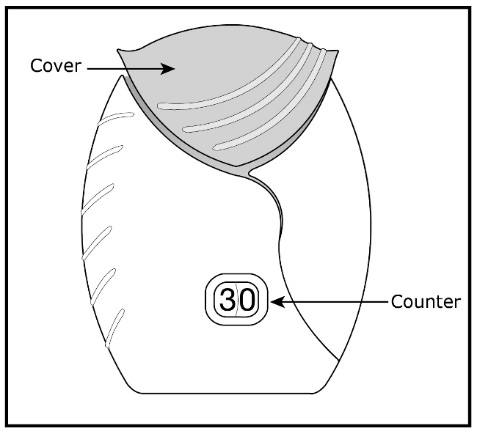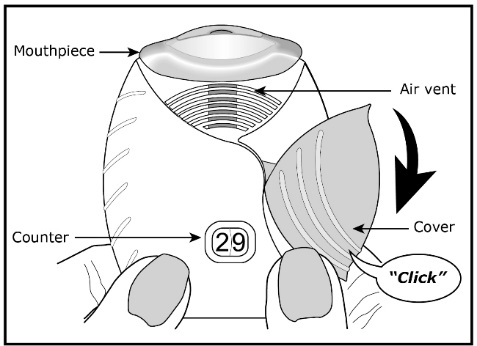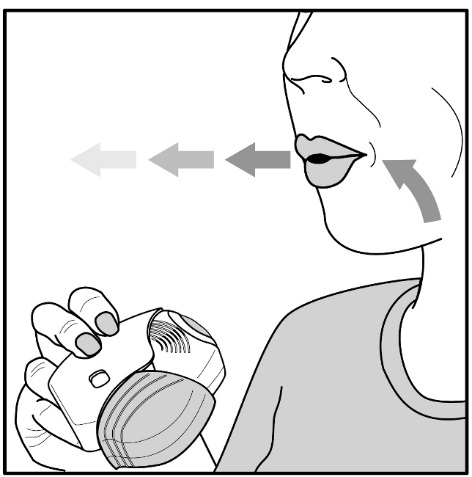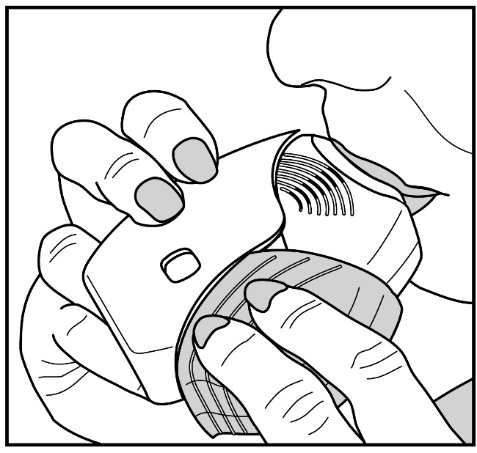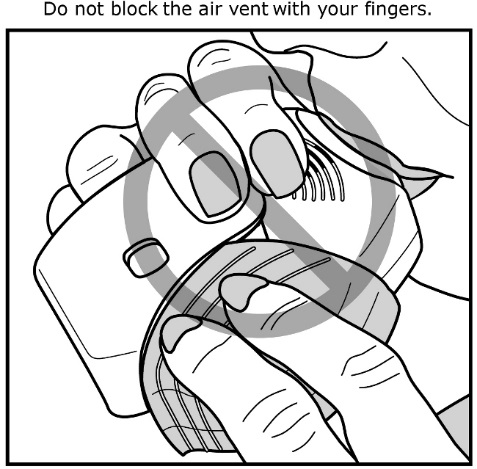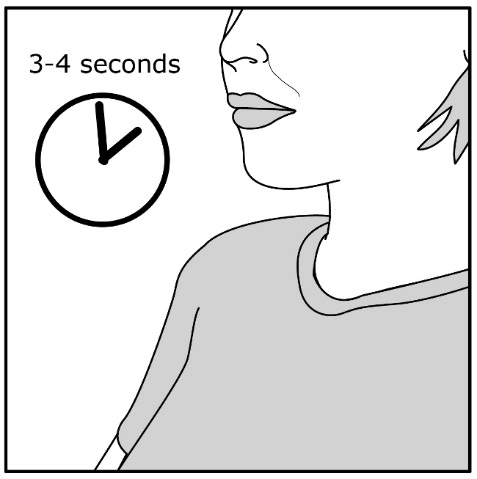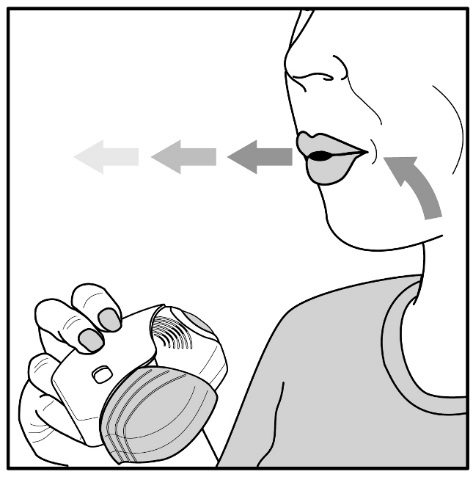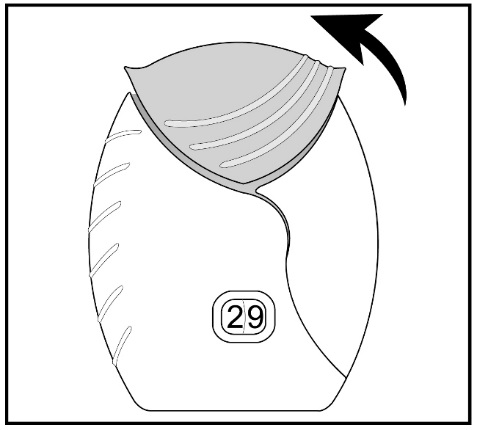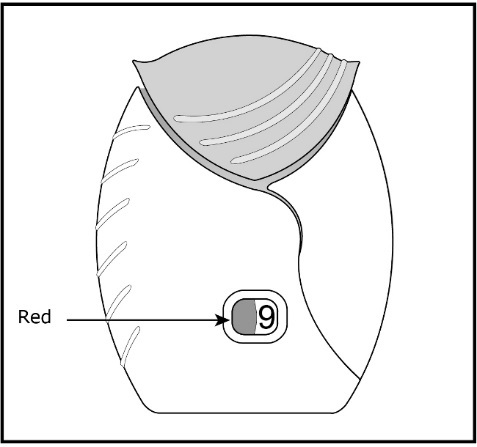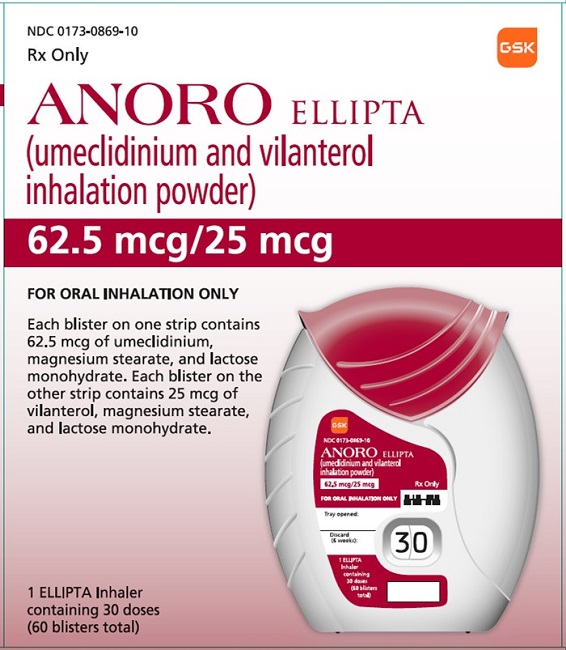 DRUG LABEL: Anoro Ellipta
NDC: 0173-0869 | Form: POWDER
Manufacturer: GlaxoSmithKline LLC
Category: prescription | Type: HUMAN PRESCRIPTION DRUG LABEL
Date: 20230602

ACTIVE INGREDIENTS: UMECLIDINIUM BROMIDE 62.5 ug/1 1; VILANTEROL TRIFENATATE 25 ug/1 1
INACTIVE INGREDIENTS: MAGNESIUM STEARATE; LACTOSE MONOHYDRATE

HIGHLIGHTS OF PRESCRIBING INFORMATION

These highlights do not include all the information needed to use ANORO ELLIPTA safely and effectively. See full prescribing information for ANORO ELLIPTA.
ANORO ELLIPTA (umeclidinium and vilanterol inhalation powder), for oral inhalation use
Initial U.S. Approval: 2013

1 INDICATIONS AND USAGE

ANORO ELLIPTA is a combination of umeclidinium, an anticholinergic, and vilanterol, a long-acting beta2-adrenergic agonist (LABA), indicated for the maintenance treatment of patients with chronic obstructive pulmonary disease (COPD). (1)

Limitations of Use: Not indicated for relief of acute bronchospasm or for the treatment of asthma. (1, 5.2)

2 DOSAGE AND ADMINISTRATION

- For oral inhalation only. (2)
- Maintenance treatment of COPD: 1 actuation of ANORO ELLIPTA once daily administered by oral inhalation. (2)

3 DOSAGE FORMS AND STRENGTHS

Inhalation powder: 62.5 mcg umeclidinium and 25 mcg vilanterol (62.5/25 mcg) per actuation. (3)

4 CONTRAINDICATIONS

- Severe hypersensitivity to milk proteins or any ingredients. (4)
- Use of a LABA, including ANORO ELLIPTA, without an inhaled corticosteroid is contraindicated in patients with asthma. (4)

5 WARNINGS AND PRECAUTIONS

- LABA monotherapy (without an inhaled corticosteroid) for asthma increases the risk of serious asthma-related events. (5.1)
- Do not initiate in acutely deteriorating COPD. Do not use to treat acute symptoms. (5.2)
- Do not use in combination with additional therapy containing a LABA because of risk of overdose. (5.3)
- If paradoxical bronchospasm occurs, discontinue ANORO ELLIPTA and institute alternative therapy. (5.5)
- Use with caution in patients with cardiovascular disorders because of beta-adrenergic stimulation. (5.7)
- Use with caution in patients with convulsive disorders, thyrotoxicosis, diabetes mellitus, and ketoacidosis. (5.8)
- Worsening of narrow-angle glaucoma may occur. Use with caution in patients with narrow-angle glaucoma and instruct patients to contact a healthcare provider immediately if symptoms occur. (5.9)
- Worsening of urinary retention may occur. Use with caution in patients with prostatic hyperplasia or bladder-neck obstruction and instruct patients to contact a healthcare provider immediately if symptoms occur. (5.10)
- Be alert to hypokalemia and hyperglycemia. (5.11)

6 ADVERSE REACTIONS

Most common adverse reactions (incidence ≥1% and more common than placebo) are pharyngitis, sinusitis, lower respiratory tract infection, constipation, diarrhea, pain in extremity, muscle spasms, neck pain, and chest pain. (6.1)

To report SUSPECTED ADVERSE REACTIONS, contact GlaxoSmithKline at 1-888-825-5249 or FDA at 1-800-FDA-1088 or www.fda.gov/medwatch.

7 DRUG INTERACTIONS

- Strong cytochrome P450 3A4 inhibitors (e.g., ketoconazole): Use with caution. May cause cardiovascular effects. (7.1)
- Monoamine oxidase inhibitors and tricyclic antidepressants: Use with extreme caution. May potentiate effect of vilanterol on cardiovascular system. (7.2)
- Beta-blockers: Use with caution. May block bronchodilatory effects of beta-agonists and produce severe bronchospasm. (7.3)
- Diuretics: Use with caution. Electrocardiographic changes and/or hypokalemia associated with non–potassium-sparing diuretics may worsen with concomitant beta-agonists. (7.4)
- Anticholinergics: May interact additively with concomitantly used anticholinergic medications. Avoid administration of ANORO ELLIPTA with other anticholinergic-containing drugs. (7.5)

FULL PRESCRIBING INFORMATION

1 INDICATIONS AND USAGE

ANORO ELLIPTA is indicated for the maintenance treatment of patients with chronic obstructive pulmonary disease (COPD).

Limitations of Use

ANORO ELLIPTA is NOT indicated for the relief of acute bronchospasm or for the treatment of asthma. The safety and effectiveness of ANORO ELLIPTA in asthma have not been established.

2 DOSAGE AND ADMINISTRATION

The recommended dosage of ANORO ELLIPTA for maintenance treatment of COPD is 62.5 mcg umeclidinium and 25 mcg vilanterol (1 actuation of ANORO ELLIPTA 62.5/25 mcg) once daily by oral inhalation.

- ANORO ELLIPTA should be used at the same time every day. Do not use ANORO ELLIPTA more than 1 time every 24 hours.
- No dosage adjustment is required for geriatric patients, patients with renal impairment, or patients with moderate hepatic impairment [see Clinical Pharmacology (12.3)].

3 DOSAGE FORMS AND STRENGTHS

Inhalation powder: 62.5 mcg umeclidinium and 25 mcg vilanterol (62.5/25 mcg) per actuation.

4 CONTRAINDICATIONS

ANORO ELLIPTA is contraindicated in:

- patients with severe hypersensitivity to milk proteins or who have demonstrated hypersensitivity to umeclidinium, vilanterol, or any of the excipients [see Warnings and Precautions (5.6), Description (11)].
- use of a long-acting beta2-adrenergic agonist (LABA), including vilanterol, one of the active ingredients in ANORO ELLIPTA, without an inhaled corticosteroid (ICS), in patients with asthma [see Warnings and Precautions (5.1)]. ANORO ELLIPTA is not indicated for the treatment of asthma.

5 WARNINGS AND PRECAUTIONS

5.1 Serious Asthma-Related Events – Hospitalizations, Intubations, Death

The safety and effectiveness of ANORO ELLIPTA in patients with asthma have not been established. ANORO ELLIPTA is not indicated for the treatment of asthma [see Contraindications (4)].

Use of LABA as monotherapy (without ICS) for asthma is associated with an increased risk of asthma-related death. Available data from controlled clinical trials also suggest that use of LABA as monotherapy increases the risk of asthma-related hospitalization in pediatric and adolescent patients. These findings are considered a class effect of LABA monotherapy. When LABA are used in fixed-dose combination with ICS, data from large clinical trials do not show a significant increase in the risk of serious asthma-related events (hospitalizations, intubations, death) compared with ICS alone.

Salmeterol Multicenter Asthma Research Trial (SMART)

A 28-week, placebo-controlled, US trial that compared the safety of another LABA (salmeterol) with placebo, each added to usual asthma therapy, showed an increase in asthma-related deaths in subjects receiving salmeterol (13/13,176 in subjects treated with salmeterol vs. 3/13,179 in subjects treated with placebo; relative risk: 4.37 [95% CI: 1.25, 15.34]). The increased risk of asthma-related death is considered a class effect of LABAs, including vilanterol, one of the active ingredients in ANORO ELLIPTA.

No trial adequate to determine whether the rate of asthma-related death is increased in subjects treated with ANORO ELLIPTA has been conducted.

Available data do not suggest an increased risk of death with use of LABA in patients with COPD.

5.2 Deterioration of Disease and Acute Episodes

ANORO ELLIPTA should not be initiated in patients during rapidly deteriorating or potentially life-threatening episodes of COPD. ANORO ELLIPTA has not been studied in subjects with acutely deteriorating COPD. The initiation of ANORO ELLIPTA in this setting is not appropriate.

If ANORO ELLIPTA no longer controls symptoms of bronchoconstriction; the patient’s inhaled, short-acting beta2-agonist becomes less effective; or the patient needs more short-acting beta2-agonist than usual, these may be markers of deterioration of disease. In this setting, re-evaluate the patient and the COPD treatment regimen at once. The daily dose of ANORO ELLIPTA should not be increased. Increasing use of inhaled, short-acting beta2-agonists is a signal of deteriorating disease. In this situation, the patient requires immediate re-evaluation with reassessment of the treatment regimen, giving special consideration to the need for additional therapeutic options. Patients should not use more than 1 inhalation of ANORO ELLIPTA once daily.

ANORO ELLIPTA should not be used for the relief of acute symptoms, i.e., as rescue therapy for the treatment of acute episodes of bronchospasm. ANORO ELLIPTA has not been studied in the relief of acute symptoms and extra doses should not be used for that purpose. Acute symptoms should be treated with an inhaled, short-acting beta2-agonist.

When beginning treatment with ANORO ELLIPTA, patients who have been taking oral or inhaled, short-acting beta2-agonists on a regular basis (e.g., 4 times a day) should be instructed to discontinue the regular use of these drugs and to use them only for symptomatic relief of acute respiratory symptoms. When prescribing ANORO ELLIPTA, the healthcare provider should also prescribe an inhaled, short-acting beta2-agonist and instruct the patient on how it should be used.

5.3 Avoid Excessive Use of ANORO ELLIPTA and Avoid Use with Other Long-acting Beta2-agonists

ANORO ELLIPTA should not be used more often than recommended, at higher doses than recommended, or in conjunction with other therapies containing LABAs, as an overdose may result. Clinically significant cardiovascular effects and fatalities have been reported in association with excessive use of inhaled sympathomimetic drugs. Patients using ANORO ELLIPTA should not use another therapy containing a LABA (e.g., salmeterol, formoterol fumarate, arformoterol tartrate, indacaterol) for any reason.

5.4 Drug Interactions with Strong Cytochrome P450 3A4 Inhibitors

Caution should be exercised when considering the coadministration of ANORO ELLIPTA with ketoconazole and other known strong cytochrome P450 3A4 (CYP3A4) inhibitors (including, but not limited to, ritonavir, clarithromycin, conivaptan, indinavir, itraconazole, lopinavir, nefazodone, nelfinavir, saquinavir, telithromycin, troleandomycin, voriconazole) because increased cardiovascular adverse effects may occur [see Drug Interactions (7.1), Clinical Pharmacology (12.3)].

5.5 Paradoxical Bronchospasm

As with other inhaled therapies, ANORO ELLIPTA can produce paradoxical bronchospasm, which may be life threatening. If paradoxical bronchospasm occurs following dosing with ANORO ELLIPTA, it should be treated immediately with an inhaled, short-acting bronchodilator; ANORO ELLIPTA should be discontinued immediately; and alternative therapy should be instituted.

5.6 Hypersensitivity Reactions, including Anaphylaxis

Hypersensitivity reactions such as anaphylaxis, angioedema, rash, and urticaria may occur after administration of ANORO ELLIPTA. Discontinue ANORO ELLIPTA if such reactions occur. There have been reports of anaphylactic reactions in patients with severe milk protein allergy after inhalation of other powder medications containing lactose; therefore, patients with severe milk protein allergy should not use ANORO ELLIPTA [see Contraindications (4), Adverse Reactions (6.2)].

5.7 Cardiovascular Effects

Vilanterol, like other beta2-agonists, can produce a clinically significant cardiovascular effect in some patients as measured by increases in pulse rate, systolic or diastolic blood pressure, and also cardiac arrhythmias, such as supraventricular tachycardia and extrasystoles. If such effects occur, ANORO ELLIPTA may need to be discontinued. In addition, beta-agonists have been reported to produce electrocardiographic changes, such as flattening of the T wave, prolongation of the QTc interval, and ST segment depression, although the clinical significance of these findings is unknown [see Clinical Pharmacology (12.2)]. Fatalities have been reported in association with excessive use of inhaled sympathomimetic drugs.

ANORO ELLIPTA, like other sympathomimetic amines, should be used with caution in patients with cardiovascular disorders, especially coronary insufficiency, cardiac arrhythmias, and hypertension.

In a 52-week trial of subjects with COPD, the exposure-adjusted rates for any on-treatment major adverse cardiac event, including non-fatal central nervous system hemorrhages and cerebrovascular conditions, non-fatal myocardial infarction, non-fatal acute myocardial infarction, and adjudicated on-treatment death due to cardiovascular events, was 2.2 per 100 patient-years for fluticasone furoate/umeclidinium/vilanterol 100/62.5/25 mcg (n = 4,151), 1.9 per 100 patient-years for fluticasone furoate/vilanterol 100/25 mcg (n = 4,134), and 2.2 per 100 patient-years for ANORO ELLIPTA (n = 2,070). Adjudicated on‑treatment deaths due to cardiovascular events occurred in 20 of 4,151 patients (0.54 per 100 patient-years) receiving fluticasone furoate/umeclidinium/vilanterol, 27 of 4,134 patients (0.78 per 100 patient-years) receiving fluticasone furoate/vilanterol, and 16 of 2,070 patients (0.94 per 100 patient-years) receiving ANORO ELLIPTA.

5.8 Coexisting Conditions

ANORO ELLIPTA, like all therapies containing sympathomimetic amines, should be used with caution in patients with convulsive disorders or thyrotoxicosis and in those who are unusually responsive to sympathomimetic amines. Doses of the related beta2-adrenoceptor agonist albuterol, when administered intravenously, have been reported to aggravate preexisting diabetes mellitus and ketoacidosis.

5.9 Worsening of Narrow-Angle Glaucoma

ANORO ELLIPTA should be used with caution in patients with narrow-angle glaucoma. Prescribers and patients should also be alert for signs and symptoms of acute narrow-angle glaucoma (e.g., eye pain or discomfort, blurred vision, visual halos, or colored images in association with red eyes from conjunctival congestion and corneal edema). Instruct patients to consult a healthcare provider immediately if any of these signs or symptoms develop.

5.10 Worsening of Urinary Retention

ANORO ELLIPTA, like all therapies containing an anticholinergic, should be used with caution in patients with urinary retention. Prescribers and patients should be alert for signs and symptoms of urinary retention (e.g., difficulty passing urine, painful urination), especially in patients with prostatic hyperplasia or bladder-neck obstruction. Instruct patients to consult a healthcare provider immediately if any of these signs or symptoms develop.

5.11 Hypokalemia and Hyperglycemia

Beta-adrenergic agonist therapies may produce significant hypokalemia in some patients, possibly through intracellular shunting, which has the potential to produce adverse cardiovascular effects. The decrease in serum potassium is usually transient, not requiring supplementation. Beta-agonist therapies may produce transient hyperglycemia in some patients. In 4 clinical trials of 6-month duration evaluating ANORO ELLIPTA in subjects with COPD, there was no evidence of a treatment effect on serum glucose or potassium.

6 ADVERSE REACTIONS

The following clinically significant adverse reactions are described elsewhere in labeling:

- Serious asthma-related events–hospitalizations, intubations, death [see Warnings and Precautions (5.1)]
- Paradoxical bronchospasm [see Warnings and Precautions (5.5)]
- Cardiovascular effects [see Warnings and Precautions (5.7)]
- Worsening of narrow-angle glaucoma [see Warnings and Precautions (5.9)]
- Worsening of urinary retention [see Warnings and Precautions (5.10)]

6.1 Clinical Trials Experience

Because clinical trials are conducted under widely varying conditions, adverse reaction rates observed in the clinical trials of a drug cannot be directly compared with rates in the clinical trials of another drug and may not reflect the rates observed in practice.

The clinical program for ANORO ELLIPTA included 8,138 subjects with COPD in four 6‑month lung function trials, one 12-month long-term safety study, and 9 other trials of shorter duration. A total of 1,124 subjects have received at least 1 dose of ANORO ELLIPTA (umeclidinium/vilanterol 62.5/25 mcg), and 1,330 subjects have received a higher dose of umeclidinium/vilanterol (125/25 mcg). The safety data described below are based on the four 6-month and one 12-month trials. Adverse reactions observed in the other trials were similar to those observed in the confirmatory trials.

6-Month Trials

The incidence of adverse reactions associated with ANORO ELLIPTA in Table 1 is based on four 6-month trials: 2 placebo-controlled trials (Trial 1 and Trial 2); N = 1,532 and N = 1,489, respectively) and 2 active-controlled trials (Trial 3 and Trial 4); N = 843 and N = 869, respectively). Of the 4,733 subjects, 68% were male and 84% were white. They had a mean age of 63 years and an average smoking history of 45 pack-years, with 50% identified as current smokers. At screening, the mean postbronchodilator percent predicted forced expiratory volume in 1 second (FEV1) was 48% (range: 13% to 76%), the mean postbronchodilator FEV1/forced vital capacity (FVC) ratio was 0.47 (range: 0.13 to 0.78), and the mean percent reversibility was 14% (range: -45% to 109%).

Subjects received 1 dose once daily of the following: ANORO ELLIPTA, umeclidinium/vilanterol 125/25 mcg, umeclidinium 62.5 mcg, umeclidinium 125 mcg, vilanterol 25 mcg, active control, or placebo.

Table 1. Adverse Reactions with ANORO ELLIPTA with ≥1% Incidence and More Common than Placebo in Subjects with Chronic Obstructive Pulmonary Disease
Adverse Reaction | ANORO ELLIPTA; (n = 842); % | Umeclidinium; 62.5 mcg; (n = 418); % | Vilanterol; 25 mcg; (n = 1,034); % | Placebo; (n = 555); %
Infections and infestations
Pharyngitis | 2 | 1 | 2 | <1
Sinusitis | 1 | <1 | 1 | <1
Lower respiratory tract infection | 1 | <1 | <1 | <1
Gastrointestinal disorders
Constipation | 1 | <1 | <1 | <1
Diarrhea | 2 | <1 | 2 | 1
Musculoskeletal and connective tissue disorders
Pain in extremity | 2 | <1 | 2 | 1
Muscle spasms | 1 | <1 | <1 | <1
Neck pain | 1 | <1 | <1 | <1
General disorders and administration site conditions
Chest pain | 1 | <1 | <1 | <1

Other adverse reactions with ANORO ELLIPTA observed with an incidence <1% but more common than placebo included the following: productive cough, dry mouth, dyspepsia, abdominal pain, gastroesophageal reflux disease, vomiting, musculoskeletal chest pain, chest discomfort, asthenia, atrial fibrillation, ventricular extrasystoles, supraventricular extrasystoles, myocardial infarction, pruritus, rash, and conjunctivitis.

12-Month Trial

In a long-term safety trial (Trial 5), 335 subjects were treated for up to 12 months with umeclidinium/vilanterol 125/25 mcg or placebo. The demographic and baseline characteristics of the long-term safety trial were similar to those of the placebo-controlled efficacy trials described above. Adverse reactions observed with a frequency of ≥1% in the group receiving umeclidinium/vilanterol 125/25 mcg that exceeded that in placebo in this trial were: headache, back pain, sinusitis, cough, urinary tract infection, arthralgia, nausea, vertigo, abdominal pain, pleuritic pain, viral respiratory tract infection, toothache, and diabetes mellitus.

6.2 Postmarketing Experience

In addition to adverse reactions reported from clinical trials, the following adverse reactions have been identified during postapproval use of ANORO ELLIPTA. Because these reactions are reported voluntarily from a population of uncertain size, it is not always possible to reliably estimate their frequency or establish a causal relationship to drug exposure. These events have been chosen for inclusion due to either their seriousness, frequency of reporting, or causal connection to ANORO ELLIPTA or a combination of these factors.

Cardiac Disorders

Palpitations.

Eye Disorders

Blurred vision, eye pain, glaucoma, increased intraocular pressure.

Immune System Disorders

Hypersensitivity reactions, including anaphylaxis, angioedema, and urticaria.

Nervous System Disorders

Dysgeusia, tremor.

Psychiatric Disorders

Anxiety.

Renal and Urinary Disorders

Dysuria, urinary retention.

Respiratory, Thoracic, and Mediastinal Disorders

Dysphonia, paradoxical bronchospasm.

7 DRUG INTERACTIONS

7.1 Inhibitors of Cytochrome P450 3A4

Vilanterol is a substrate of CYP3A4. Concomitant administration of the strong CYP3A4 inhibitor ketoconazole increases the systemic exposure to vilanterol. Caution should be exercised when considering the coadministration of ANORO ELLIPTA with ketoconazole and other known strong CYP3A4 inhibitors [see Warnings and Precautions (5.4), Clinical Pharmacology (12.3)].

7.2 Monoamine Oxidase Inhibitors, Tricyclic Antidepressants, and QTc Prolonging Drugs

Vilanterol, like other beta2-agonists, should be administered with extreme caution to patients being treated with monoamine oxidase inhibitors, tricyclic antidepressants, or drugs known to prolong the QTc interval or within 2 weeks of discontinuation of such agents, because the effect of adrenergic agonists on the cardiovascular system may be potentiated by these agents. Drugs that are known to prolong the QTc interval have an increased risk of ventricular arrhythmias.

7.3 Beta-adrenergic Receptor Blocking Agents

Beta-blockers not only block the pulmonary effect of beta-agonists, such as vilanterol, but may also produce severe bronchospasm in patients with COPD. Therefore, patients with COPD should not normally be treated with beta-blockers. However, under certain circumstances, there may be no acceptable alternatives to the use of beta-adrenergic blocking agents for these patients; cardioselective beta-blockers could be considered, although they should be administered with caution.

7.4 Non–Potassium-Sparing Diuretics

The electrocardiographic changes and/or hypokalemia that may result from the administration of non–potassium-sparing diuretics (such as loop or thiazide diuretics) can be acutely worsened by beta-agonists, especially when the recommended dose of the beta-agonist is exceeded. Although the clinical significance of these effects is not known, caution is advised in the coadministration of beta-agonists with non–potassium-sparing diuretics.

7.5 Anticholinergics

There is potential for an additive interaction with concomitantly used anticholinergic medicines. Therefore, avoid coadministration of ANORO ELLIPTA with other anticholinergic-containing drugs as this may lead to an increase in anticholinergic adverse effects [see Warnings and Precautions (5.9, 5.10)].

8 USE IN SPECIFIC POPULATIONS

8.1 Pregnancy

Risk Summary

There are insufficient data on the use of ANORO ELLIPTA or its individual components, umeclidinium and vilanterol, in pregnant women to inform a drug-associated risk. (See Clinical Considerations.) In animal reproduction studies, umeclidinium administered via inhalation or subcutaneously to pregnant rats and rabbits was not associated with adverse effects on embryofetal development at exposures approximately 50 and 200 times, respectively, the human exposure at the maximum recommended human daily inhaled dose (MRHDID). Vilanterol administered via inhalation to pregnant rats and rabbits produced no fetal structural abnormalities at exposures approximately 70 times the MRHDID. (See Data.)

The estimated risk of major birth defects and miscarriage for the indicated populations is unknown. In the U.S. general population, the estimated risk of major birth defects and miscarriage in clinically recognized pregnancies is 2% to 4% and 15% to 20%, respectively.

Clinical Considerations

Labor or Delivery: ANORO ELLIPTA should be used during late gestation and labor only if the potential benefit justifies the potential for risks related to beta-agonists interfering with uterine contractility.

Data

Animal Data: The combination of umeclidinium and vilanterol has not been studied in pregnant animals. Studies in pregnant animals have been conducted with umeclidinium and vilanterol individually.

Umeclidinium: In separate embryofetal developmental studies, pregnant rats and rabbits received umeclidinium during the period of organogenesis at doses up to approximately 50 and 200 times the MRHDID, respectively (on an AUC basis at maternal inhalation doses up to 278 mcg/kg/day in rats and at maternal subcutaneous doses up to 180 mcg/kg/day in rabbits). No evidence of teratogenic effects was observed in either species.

In a perinatal and postnatal developmental study in rats, dams received umeclidinium during late gestation and lactation periods with no evidence of effects on offspring development at doses up to approximately 26 times the MRHDID (on an AUC basis at maternal subcutaneous doses up to 60 mcg/kg/day).

Vilanterol: In separate embryofetal developmental studies, pregnant rats and rabbits received vilanterol during the period of organogenesis at doses up to approximately 13,000 and 450 times, respectively, the MRHDID (on a mcg/m^2 basis at maternal inhalation doses up to 33,700 mcg/kg/day in rats and on an AUC basis at maternal inhaled doses up to 5,740 mcg/kg/day in rabbits). No evidence of structural abnormalities was observed at any dose in rats or in rabbits up to approximately 70 times the MRHDID (on an AUC basis at maternal doses up to 591 mcg/kg/day in rabbits). However, fetal skeletal variations were observed in rabbits at approximately 450 times the MRHDID (on an AUC basis at maternal inhaled or subcutaneous doses of 5,740 or 300 mcg/kg/day, respectively). The skeletal variations included decreased or absent ossification in cervical vertebral centrum and metacarpals.

In a perinatal and postnatal developmental study in rats, dams received vilanterol during late gestation and the lactation periods at doses up to approximately 3,900 times the MRHDID (on a mcg/m^2 basis at maternal oral doses up to 10,000 mcg/kg/day). No evidence of effects in offspring development was observed.

8.2 Lactation

Risk Summary

There is no information available on the presence of umeclidinium or vilanterol in human milk, the effects on the breastfed child, or the effects on milk production. Umeclidinium was detected in the plasma of offspring of lactating rats treated with umeclidinium suggesting its presence in maternal milk. (See Data.) The developmental and health benefits of breastfeeding should be considered along with the mother’s clinical need for ANORO ELLIPTA and any potential adverse effects on the breastfed child from umeclidinium or vilanterol or from the underlying maternal condition.

Data

Subcutaneous administration of umeclidinium to lactating rats at greater than or equal to 60 mcg/kg/day resulted in a quantifiable level of umeclidinium in 2 of 54 pups, which may indicate transfer of umeclidinium in rat milk.

8.4 Pediatric Use

The safety and effectiveness of ANORO ELLIPTA have not been established in pediatric patients. ANORO ELLIPTA is not indicated for use in pediatric patients.

8.5 Geriatric Use

Based on available data, no adjustment of the dosage of ANORO ELLIPTA in geriatric patients is necessary, but greater sensitivity in some older individuals cannot be ruled out.

Clinical trials of ANORO ELLIPTA for COPD included 2,143 subjects aged 65 years and older and 478 subjects aged 75 years and older. No overall differences in safety or effectiveness were observed between these subjects and younger subjects, and other reported clinical experience has not identified differences in responses between the elderly and younger subjects.

8.6 Hepatic Impairment

Patients with moderate hepatic impairment (Child-Pugh score of 7-9) showed no relevant increases in Cmax or AUC, nor did protein binding differ between subjects with moderate hepatic impairment and their healthy controls. Studies in subjects with severe hepatic impairment have not been performed [see Clinical Pharmacology (12.3)].

8.7 Renal Impairment

There were no significant increases in either umeclidinium or vilanterol exposure in subjects with severe renal impairment (CrCl <30 mL/min) compared with healthy subjects. No dosage adjustment is required in patients with renal impairment [see Clinical Pharmacology (12.3)].

10 OVERDOSAGE

ANORO ELLIPTA contains both umeclidinium and vilanterol; therefore, the risks associated with overdosage for the individual components described below apply to ANORO ELLIPTA. Treatment of overdosage consists of discontinuation of ANORO ELLIPTA together with institution of appropriate symptomatic and/or supportive therapy. The judicious use of a cardioselective beta-receptor blocker may be considered, bearing in mind that such medicine can produce bronchospasm. Cardiac monitoring is recommended in cases of overdosage.

Umeclidinium

High doses of umeclidinium may lead to anticholinergic signs and symptoms.

Vilanterol

The expected signs and symptoms with overdosage of vilanterol are those of excessive beta-adrenergic stimulation and/or occurrence or exaggeration of any of the signs and symptoms of beta-adrenergic stimulation (e.g., seizures, angina, hypertension or hypotension, tachycardia with rates up to 200 beats/min, arrhythmias, nervousness, headache, tremor, muscle cramps, dry mouth, palpitation, nausea, dizziness, fatigue, malaise, insomnia, hyperglycemia, hypokalemia, metabolic acidosis). As with all inhaled sympathomimetic medicines, cardiac arrest and even death may be associated with an overdose of vilanterol.

11 DESCRIPTION

ANORO ELLIPTA is an inhalation powder drug product for delivery of a combination of umeclidinium (an anticholinergic) and vilanterol (a LABA) to patients by oral inhalation.

Umeclidinium bromide has the chemical name 1-[2-(benzyloxy)ethyl]-4-(hydroxydiphenylmethyl)-1-azoniabicyclo[2.2.2]octane bromide and the following chemical structure:

Umeclidinium bromide is a white powder with a molecular weight of 508.5, and the empirical formula is C29H34NO2•Br (as a quaternary ammonium bromide compound). It is slightly soluble in water.

Vilanterol trifenatate has the chemical name triphenylacetic acid-4-{(1R)-2-[(6-{2-[(2,6-dicholorobenzyl)oxy]ethoxy}hexyl)amino]-1-hydroxyethyl}-2-(hydroxymethyl)phenol (1:1) and the following chemical structure:

Vilanterol trifenatate is a white powder with a molecular weight of 774.8, and the empirical formula is C24H33Cl2NO5•C20H16O2. It is practically insoluble in water.

ANORO ELLIPTA is a light grey and red plastic inhaler containing 2 foil blister strips. Each blister on one strip contains a white powder blend of micronized umeclidinium bromide (74.2 mcg equivalent to 62.5 mcg of umeclidinium), magnesium stearate (75 mcg), and lactose monohydrate (to 12.5 mg), and each blister on the other strip contains a white powder blend of micronized vilanterol trifenatate (40 mcg equivalent to 25 mcg of vilanterol), magnesium stearate (125 mcg), and lactose monohydrate (to 12.5 mg). The lactose monohydrate contains milk proteins. After the inhaler is activated, the powder within both blisters is exposed and ready for dispersion into the airstream created by the patient inhaling through the mouthpiece.

Under standardized in vitro test conditions, ANORO ELLIPTA delivers 55 mcg of umeclidinium and 22 mcg of vilanterol per dose when tested at a flow rate of 60 L/min for 4 seconds.

In adult subjects with obstructive lung disease and severely compromised lung function (COPD with FEV1/FVC <70% and FEV1 <30% predicted or FEV1 <50% predicted plus chronic respiratory failure), mean peak inspiratory flow through the ELLIPTA inhaler was 66.5 L/min (range: 43.5 to 81.0 L/min).

The actual amount of drug delivered to the lung will depend on patient factors, such as inspiratory flow profile.

12 CLINICAL PHARMACOLOGY

12.1 Mechanism of Action

ANORO ELLIPTA

ANORO ELLIPTA contains both umeclidinium and vilanterol. The mechanisms of action described below for the individual components apply to ANORO ELLIPTA. These drugs represent 2 different classes of medications (an anticholinergic and a LABA) each having different effects on clinical and physiological indices.

Umeclidinium

Umeclidinium is a long-acting muscarinic antagonist, which is often referred to as an anticholinergic. It has similar affinity to the subtypes of muscarinic receptors M1 to M5. In the airways, it exhibits pharmacological effects through inhibition of M3 receptor at the smooth muscle leading to bronchodilation. The competitive and reversible nature of antagonism was shown with human and animal origin receptors and isolated organ preparations. In preclinical in vitro as well as in vivo studies, prevention of methacholine- and acetylcholine-induced bronchoconstrictive effects was dose-dependent and lasted longer than 24 hours. The clinical relevance of these findings is unknown. The bronchodilation following inhalation of umeclidinium is predominantly a site-specific effect.

Vilanterol

Vilanterol is a LABA. In vitro tests have shown the functional selectivity of vilanterol was similar to salmeterol. The clinical relevance of this in vitro finding is unknown.

Although beta2-receptors are the predominant adrenergic receptors in bronchial smooth muscle and beta1-receptors are the predominant receptors in the heart, there are also beta2-receptors in the human heart comprising 10% to 50% of the total beta-adrenergic receptors. The precise function of these receptors has not been established, but they raise the possibility that even highly selective beta2-agonists may have cardiac effects.

The pharmacologic effects of beta2-adrenergic agonist drugs, including vilanterol, are at least in part attributable to stimulation of intracellular adenyl cyclase, the enzyme that catalyzes the conversion of adenosine triphosphate (ATP) to cyclic-3′,5′-adenosine monophosphate (cyclic AMP). Increased cyclic AMP levels cause relaxation of bronchial smooth muscle and inhibition of release of mediators of immediate hypersensitivity from cells, especially from mast cells.

12.2 Pharmacodynamics

Cardiac Electrophysiology

Healthy Subjects: QTc interval prolongation was studied in a double-blind, multiple-dose, placebo- and positive-controlled crossover study in 86 healthy subjects. The maximum mean (95% upper confidence bound) difference in QTcF from placebo after baseline correction was 4.6 (7.1) milliseconds and 8.2 (10.7) milliseconds for umeclidinium/vilanterol 125/25 mcg and umeclidinium/vilanterol 500/100 mcg (8/4 times the recommended dosage), respectively.

A dose-dependent increase in heart rate was also observed. The maximum mean (95% upper confidence bound) difference in heart rate from placebo after baseline correction was 8.8 (10.5) beats/min and 20.5 (22.3) beats/min seen 10 minutes after dosing for umeclidinium/vilanterol 125/25 mcg and umeclidinium/vilanterol 500/100 mcg, respectively.

Subjects with Chronic Obstructive Pulmonary Disease: The effect of ANORO ELLIPTA on cardiac rhythm in subjects diagnosed with COPD was assessed using 24-hour Holter monitoring in 6- and 12-month trials: 53 subjects received ANORO ELLIPTA, 281 subjects received umeclidinium/vilanterol 125/25 mcg, and 182 subjects received placebo. No clinically meaningful effects on cardiac rhythm were observed.

12.3 Pharmacokinetics

Linear pharmacokinetics was observed for umeclidinium (62.5 to 500 mcg) and vilanterol (25 to 100 mcg).

Absorption

Umeclidinium: Umeclidinium plasma levels may not predict therapeutic effect. Following inhaled administration of umeclidinium in healthy subjects, Cmax occurred at 5 to 15 minutes. Umeclidinium is mostly absorbed from the lung after inhaled doses with minimum contribution from oral absorption. Following repeat dosing of inhaled ANORO ELLIPTA, steady state was achieved within 14 days with up to 1.8-fold accumulation.

Vilanterol: Vilanterol plasma levels may not predict therapeutic effect. Following inhaled administration of vilanterol in healthy subjects, Cmax occurred at 5 to 15 minutes. Vilanterol is mostly absorbed from the lung after inhaled doses with negligible contribution from oral absorption. Following repeat dosing of inhaled ANORO ELLIPTA, steady state was achieved within 14 days with up to 1.7-fold accumulation.

Distribution

Umeclidinium: Following intravenous administration to healthy subjects, the mean volume of distribution was 86 L. In vitro plasma protein binding in human plasma was on average 89%.

Vilanterol: Following intravenous administration to healthy subjects, the mean volume of distribution at steady state was 165 L. In vitro plasma protein binding in human plasma was on average 94%.

Elimination

Metabolism: Umeclidinium: In vitro data showed that umeclidinium is primarily metabolized by the enzyme cytochrome P450 2D6 (CYP2D6) and is a substrate for the P-glycoprotein (P-gp) transporter. The primary metabolic routes for umeclidinium are oxidative (hydroxylation, O-dealkylation) followed by conjugation (e.g., glucuronidation), resulting in a range of metabolites with either reduced pharmacological activity or for which the pharmacological activity has not been established. Systemic exposure to the metabolites is low.

Vilanterol: In vitro data showed that vilanterol is metabolized principally by CYP3A4 and is a substrate for the P-gp transporter. Vilanterol is metabolized to a range of metabolites with significantly reduced β1- and β2-agonist activity.

Excretion: Umeclidinium: The effective half-life after once-daily oral dosing is 11 hours. Following intravenous dosing with radiolabeled umeclidinium, mass balance showed 58% of the radiolabel in the feces and 22% in the urine. The excretion of the drug-related material in the feces following intravenous dosing indicated elimination in the bile. Following oral dosing to healthy male subjects, radiolabel recovered in feces was 92% of the total dose and that in urine was <1% of the total dose, suggesting negligible oral absorption.

Vilanterol: The effective half-life for vilanterol, as determined from inhalation administration of multiple doses, is 11 hours. Following oral administration of radiolabeled vilanterol, mass balance showed 70% of the radiolabel in the urine and 30% in the feces.

Specific Populations

The effects of renal and hepatic impairment and other intrinsic factors on the pharmacokinetics of umeclidinium and vilanterol are shown in Figure 1. Population pharmacokinetic analysis showed no evidence of a clinically significant effect of age (40 to 93 years) (Figure 1), gender (69% male) (Figure 1), inhaled corticosteroid use (48%), or weight (34 to 161 kg) on systemic exposure of either umeclidinium or vilanterol. In addition, there was no evidence of a clinically significant effect of race.

Figure 1. Impact of Intrinsic Factors on the Pharmacokinetics (PK) of Umeclidinium (UMEC) and Vilanterol (VI)

Patients with Hepatic Impairment: The impact of hepatic impairment on the pharmacokinetics of ANORO ELLIPTA has been evaluated in subjects with moderate hepatic impairment (Child-Pugh score of 7-9). There was no evidence of an increase in systemic exposure to either umeclidinium or vilanterol (Cmax and AUC) (Figure 1). There was no evidence of altered protein binding in subjects with moderate hepatic impairment compared with healthy subjects. ANORO ELLIPTA has not been evaluated in subjects with severe hepatic impairment.

Patients with Renal Impairment: The pharmacokinetics of ANORO ELLIPTA has been evaluated in subjects with severe renal impairment (CrCl <30 mL/min). Umeclidinium systemic exposure was not increased and vilanterol systemic exposure (AUC(0-24)) was 56% higher in subjects with severe renal impairment compared with healthy subjects (Figure 1). There was no evidence of altered protein binding in subjects with severe renal impairment compared with healthy subjects.

Drug Interaction Studies

When umeclidinium and vilanterol were administered in combination by the inhaled route, the pharmacokinetic parameters for each component were similar to those observed when each active substance was administered separately.

Inhibitors of Cytochrome P450 3A4: Vilanterol is a substrate of CYP3A4. A double-blind, repeat-dose, 2-way crossover drug interaction trial was conducted in healthy subjects to investigate the pharmacokinetic and pharmacodynamic effects of vilanterol 25 mcg as an inhalation powder with ketoconazole 400 mg. The plasma concentrations of vilanterol were higher after single and repeated doses when coadministered with ketoconazole than with placebo (Figure 2). The increase in vilanterol exposure was not associated with an increase in beta-agonist–related systemic effects on heart rate or blood potassium.

Inhibitors of Cytochrome P450 2D6: In vitro metabolism of umeclidinium is mediated primarily by CYP2D6. However, no clinically meaningful difference in systemic exposure to umeclidinium (500 mcg) (8 times the approved dose) was observed following repeat daily inhaled dosing in CYP2D6 normal (ultrarapid, extensive, and intermediate metabolizers) and poor metabolizer subjects (Figure 1).

Inhibitors of P-glycoprotein: Umeclidinium and vilanterol are both substrates of P-gp. The effect of the moderate P-gp transporter inhibitor verapamil (240 mg once daily) on the steady-state pharmacokinetics of umeclidinium and vilanterol was assessed in healthy subjects. No effect on umeclidinium or vilanterol Cmax was observed; however, an approximately 1.4-fold increase in umeclidinium AUC was observed with no effect on vilanterol AUC (Figure 2).

Figure 2. Impact of Extrinsic Factors on the Pharmacokinetics (PK) of Umeclidinium (UMEC) and Vilanterol (VI)

13 NONCLINICAL TOXICOLOGY

13.1 Carcinogenesis, Mutagenesis, Impairment of Fertility

ANORO ELLIPTA

No studies of carcinogenicity, mutagenicity, or impairment of fertility were conducted with ANORO ELLIPTA; however, studies are available for the individual components, umeclidinium and vilanterol, as described below.

Umeclidinium

Umeclidinium produced no treatment-related increases in the incidence of tumors in 2-year inhalation studies in rats and mice at inhaled doses up to 137 and 295/200 mcg/kg/day (male/female), respectively (approximately 20 and 25/20 times, respectively, the MRHDID for adults on an AUC basis).

Umeclidinium tested negative in the following genotoxicity assays: the in vitro Ames assay, in vitro mouse lymphoma assay, and in vivo rat bone marrow micronucleus assay.

No evidence of impairment of fertility was observed in male and female rats at subcutaneous doses up to 180 mcg/kg/day and at inhaled doses up to 294 mcg/kg/day, respectively (approximately 100 and 50 times, respectively, the MRHDID for adults on an AUC basis).

Vilanterol

In a 2-year carcinogenicity study in mice, vilanterol caused a statistically significant increase in ovarian tubulostromal adenomas in females at an inhaled dose of 29,500 mcg/kg/day (approximately 7,800 times the MRHDID for adults on an AUC basis). No increase in tumors was seen at an inhaled dose of 615 mcg/kg/day (approximately 210 times the MRHDID for adults on an AUC basis).

In a 2-year carcinogenicity study in rats, vilanterol caused statistically significant increases in mesovarian leiomyomas in females and shortening of the latency of pituitary tumors at inhaled doses greater than or equal to 84.4 mcg/kg/day (greater than or equal to approximately 20 times the MRHDID for adults on an AUC basis). No tumors were seen at an inhaled dose of 10.5 mcg/kg/day (approximately equal to the MRHDID for adults on an AUC basis).

These tumor findings in rodents are similar to those reported previously for other beta-adrenergic agonist drugs. The relevance of these findings to human use is unknown.

Vilanterol tested negative in the following genotoxicity assays: the in vitro Ames assay, in vivo rat bone marrow micronucleus assay, in vivo rat unscheduled DNA synthesis (UDS) assay, and in vitro Syrian hamster embryo (SHE) cell assay. Vilanterol tested equivocal in the in vitro mouse lymphoma assay.

No evidence of impairment of fertility was observed in male and female rats at inhaled vilanterol doses up to 31,500 and 37,100 mcg/kg/day, respectively (both approximately 5,490 times the MRHDID based on AUC).

14 CLINICAL STUDIES

The safety and effectiveness of ANORO ELLIPTA were evaluated in a clinical development program that included 6 dose-ranging trials, 4 lung function trials of 6 months’ duration (2 placebo controlled and 2 active controlled), two 12-week crossover trials, and a 12-month long‑term safety trial. The efficacy of ANORO ELLIPTA is based primarily on the dose-ranging trials in 1,908 subjects with COPD or asthma [see Clinical Studies (14.1)] and the 2 placebo-controlled confirmatory trials, with additional support from the 2 active-controlled and 2 crossover trials in 5,388 subjects with COPD, including chronic bronchitis and/or emphysema [see Clinical Studies (14.2)]. Evidence of efficacy for ANORO ELLIPTA on COPD exacerbations was established by the efficacy of the umeclidinium component as part of a fixed-dose combination with an ICS/LABA, as assessed in a 12-month trial in 10,355 subjects [see Clinical Studies (14.2)].

14.1 Dose-Ranging Trials

Dose selection for ANORO ELLIPTA in COPD was based on dose-ranging trials for the individual components, vilanterol and umeclidinium. Based on the findings from these studies, once-daily doses of umeclidinium/vilanterol 62.5/25 mcg and umeclidinium/vilanterol 125/25 mcg were evaluated in the confirmatory COPD trials. ANORO ELLIPTA is not indicated for asthma.

Umeclidinium

Dose selection for umeclidinium in COPD was supported by a 7-day, randomized, double-blind, placebo-controlled, crossover trial evaluating 4 doses of umeclidinium (15.6 to 125 mcg) or placebo dosed once daily in the morning in 163 subjects with COPD. A dose ordering was observed, with the 62.5- and 125-mcg doses demonstrating larger improvements in FEV1 over 24 hours compared with the lower doses of 15.6 and 31.25 mcg (Figure 3).

The differences in trough FEV1 from baseline after 7 days for placebo and the 15.6-, 31.25-, 62.5-, and 125-mcg doses were -74 mL (95% CI: -118, -31), 38 mL (95% CI: -6, 83), 27 mL (95% CI: -18, 72), 49 mL (95% CI: 6, 93), and 109 mL (95% CI: 65, 152), respectively. Two additional dose-ranging trials in subjects with COPD demonstrated minimal additional benefit at doses above 125 mcg. The dose-ranging results supported the evaluation of 2 doses of umeclidinium, 62.5 and 125 mcg, in the confirmatory COPD trials to further assess dose response.

Evaluations of dosing interval by comparing once- and twice-daily dosing supported selection of a once-daily dosing interval for further evaluation in the confirmatory COPD trials.

Figure 3. Least Squares (LS) Mean Change from Baseline in Postdose Serial FEV1 (mL) on Days 1 and 7

Day 1

Day 7

Vilanterol

Dose selection for vilanterol in COPD was supported by a 28-day, randomized, double-blind, placebo-controlled, parallel-group trial evaluating 5 doses of vilanterol (3 to 50 mcg) or placebo dosed in the morning in 602 subjects with COPD. Results demonstrated dose-related increases from baseline in FEV1 at Day 1 and Day 28 (Figure 4).

Figure 4. Least Squares (LS) Mean Change from Baseline in Postdose Serial FEV1 (0-24 h) (mL) on Days 1 and 28

Day 1

Day 28

The differences in trough FEV1 after Day 28 from baseline for placebo and the 3-, 6.25-, 12.5-, 25-, and 50-mcg doses were 29 mL (95% CI: -8, 66), 120 mL (95% CI: 83, 158), 127 mL (95% CI: 90, 164), 138 mL (95% CI: 101, 176), 166 mL (95% CI: 129, 203), and 194 mL (95% CI: 156, 231), respectively. These results supported the evaluation of vilanterol 25 mcg in the confirmatory trials for COPD.

Dose-ranging trials in subjects with asthma evaluated doses from 3 to 50 mcg and 12.5 mcg once-daily versus 6.25 mcg twice-daily dosing frequency. The results supported the selection of the vilanterol 25 mcg once-daily dose for further evaluation in the confirmatory trials for COPD.

14.2 Confirmatory Trials

Lung Function

The clinical development program for ANORO ELLIPTA included two 6-month, randomized, double-blind, placebo-controlled, parallel-group trials; two 6-month active-controlled trials; and two 12-week crossover trials in subjects with COPD designed to evaluate the efficacy of ANORO ELLIPTA on lung function. The 6-month trials treated 4,733 subjects that had a clinical diagnosis of COPD, were 40 years of age or older, had a history of smoking ≥10 pack-years, had a post-albuterol FEV1 ≤70% of predicted normal values, had a ratio of FEV1/FVC of <0.7, and had a Modified Medical Research Council (mMRC) score ≥2. Of the 4,713 subjects included in the efficacy analysis, 68% were male and 84% were white. They had a mean age of 63 years and an average smoking history of 45 pack-years, with 50% identified as current smokers. At screening, the mean postbronchodilator percent predicted FEV1 was 48% (range: 13% to 76%), the mean postbronchodilator FEV1/FVC ratio was 0.47 (range: 0.13 to 0.78), and the mean percent reversibility was 14% (range: -36% to 109%).

Trial 1 (NCT01313650) evaluated ANORO ELLIPTA (umeclidinium/vilanterol 62.5/25 mcg), umeclidinium 62.5 mcg, vilanterol 25 mcg, and placebo. The primary endpoint was change from baseline in trough (predose) FEV1 at Day 169 (defined as the mean of the FEV1 values obtained at 23 and 24 hours after the previous dose on Day 168) compared with placebo, umeclidinium 62.5 mcg, and vilanterol 25 mcg. The comparison of ANORO ELLIPTA with umeclidinium 62.5 mcg and vilanterol 25 mcg was assessed to evaluate the contribution of the individual comparators to ANORO ELLIPTA. ANORO ELLIPTA demonstrated a larger increase in mean change from baseline in trough (predose) FEV1 relative to placebo, umeclidinium 62.5 mcg, and vilanterol 25 mcg (Table 2).

Table 2. Least Squares Mean Change from Baseline in Trough FEV1 (mL) at Day 169 in the Intent-to-Treat Population (Trial 1)
Treatment | n | Trough FEV1 (mL) at Day 169
Treatment | n | Difference from
Treatment | n | Placebo; (95% CI); n = 280 | Umeclidinium; 62.5 mcga; (95% CI); n = 418 | Vilanterol; 25 mcga; (95% CI); n = 421
ANORO ELLIPTA | 413 | 167; (128, 207) | 52; (17, 87) | 95; (60, 130)
n = Number in intent-to-treat population.
a The umeclidinium and vilanterol comparators used the same inhaler and excipients as ANORO ELLIPTA.

Trial 2 (NCT01313637) had a similar study design as Trial 1 but evaluated umeclidinium/vilanterol 125/25 mcg, umeclidinium 125 mcg, vilanterol 25 mcg, and placebo. Results for umeclidinium/vilanterol 125/25 mcg in Trial 2 were similar to those observed for ANORO ELLIPTA in Trial 1.

Results from the 2 active-controlled trials and the two 12-week trials provided additional support for the efficacy of ANORO ELLIPTA in terms of change from baseline in trough FEV1 compared with the single-ingredient comparators and placebo.

Serial spirometric evaluations throughout the 24-hour dosing interval were performed in a subset of subjects (n = 197) at Days 1, 84, and 168 in Trial 1. Results from Trial 1 at Day 1 and Day 168 are shown in Figure 5.

Figure 5. Least Squares (LS) Mean Change from Baseline in FEV1 (mL) over Time (0-24 h) on Days 1 and 168 (Trial 1 Subset Population)

Day 1

Day 168

The peak FEV1 was defined as the maximum FEV1 recorded within 6 hours after the dose of trial medicine on Days 1, 28, 84, and 168 (measurements recorded at 15 and 30 minutes and 1, 3, and 6 hours). The mean peak FEV1 improvement from baseline for ANORO ELLIPTA compared with placebo at Day 1 and at Day 168 was 167 and 224 mL, respectively. The median time to onset on Day 1, defined as a 100-mL increase from baseline in FEV1, was 27 minutes in subjects receiving ANORO ELLIPTA.

Exacerbations

In Trial 6 (NCT02164513), a total of 10,355 subjects with COPD with a history of 1 or more moderate or severe exacerbations in the prior 12 months were randomized (1:2:2) to receive ANORO ELLIPTA (n = 2,070), fluticasone furoate/umeclidinium/vilanterol 100/62.5/25 mcg (n = 4,151), or fluticasone furoate/vilanterol 100/25 mcg (n = 4,134) administered once daily in a 12-month trial. The population demographics across all treatments were: mean age of 65 years, 77% white, 66% male, and an average smoking history of 46.6 pack-years, with 35% identified as current smokers. At trial entry, the most common COPD medications were ICS + anticholinergic + LABA (34%), ICS + LABA (26%), anticholinergic + LABA (8%), and anticholinergic (7%). The mean postbronchodilator percent predicted FEV1 was 46% (standard deviation: 15%), the mean postbronchodilator FEV1/FVC ratio was 0.47 (standard deviation: 0.12), and the mean percent reversibility was 10% (range: -59% to 125%).

The primary endpoint was annual rate of on-treatment moderate and severe exacerbations in subjects treated with fluticasone furoate/umeclidinium/vilanterol compared with the fixed-dose combinations of fluticasone furoate/vilanterol and ANORO ELLIPTA. Exacerbations were defined as worsening of 2 or more major symptoms (dyspnea, sputum volume, and sputum purulence) or worsening of any 1 major symptom together with any 1 of the following minor symptoms: sore throat, colds (nasal discharge and/or nasal congestion), fever without other cause, and increased cough or wheeze for at least 2 consecutive days. Exacerbations were considered to be of moderate severity if treatment with systemic corticosteroids and/or antibiotics was required and were considered to be severe if resulted in hospitalization or death.

Contribution of Umeclidinium on COPD Exacerbations: Evidence of efficacy for ANORO ELLIPTA on COPD exacerbations was established by the efficacy of the umeclidinium component of fluticasone furoate/umeclidinium/vilanterol in Trial 6. Treatment with fluticasone furoate/umeclidinium/vilanterol statistically significantly reduced the on-treatment annual rate of moderate/severe exacerbations by 15% compared with fluticasone furoate/vilanterol (Table 3). A reduction in risk of on-treatment moderate/severe exacerbation (as measured by time to first) was also observed for the same comparison. The benefit of umeclidinium on exacerbations is not expected to diminish when combined with vilanterol in ANORO ELLIPTA.

ANORO ELLIPTA and COPD Exacerbations: In Trial 6, the primary efficacy analysis of the rate of moderate/severe exacerbations, treatment with fluticasone furoate/umeclidinium/vilanterol statistically significantly reduced the on-treatment annual rate of moderate/severe exacerbations by 25% compared with ANORO ELLIPTA (Table 3).

Table 3. Moderate and Severe Chronic Obstructive Pulmonary Disease Exacerbations (Trial 6)a
Treatment | n | Mean Annual Rate; (exacerbations/year) | FF/UMEC/VI Rate Ratio vs. Comparator; (95% CI) | % Reduction in Exacerbation Rate; (95% CI) | P Value
FF/UMEC/VI | 4,145 | 0.91
FF/VI | 4,133 | 1.07 | 0.85; (0.80, 0.90) | 15; (10, 20) | P<0.001
ANORO ELLIPTA | 2,069 | 1.21 | 0.75; (0.70, 0.81) | 25; (19, 30) | P<0.001
FF/UMEC/VI = Fluticasone furoate/umeclidinium/vilanterol 100/62.5/25 mcg, FF/VI = Fluticasone furoate/vilanterol 100/25 mcg, ANORO ELLIPTA = Umeclidinium/vilanterol 62.5/25 mcg.
a On-treatment analyses excluded exacerbation data collected after discontinuation of study treatment.

16 HOW SUPPLIED/STORAGE AND HANDLING

ANORO ELLIPTA is supplied as a disposable light grey and red plastic inhaler containing 2 foil strips, each with 30 blisters (or 7 blisters for the institutional pack). One strip contains umeclidinium (62.5 mcg per blister), and the other strip contains vilanterol (25 mcg per blister). A blister from each strip is used to create 1 dose. The inhaler is packaged in a moisture-protective foil tray with a desiccant and a peelable lid in the following packs:

NDC 0173-0869-10 30 inhalations (60 blisters)

NDC 0173-0869-06 7 inhalations (14 blisters), institutional pack

Store at room temperature between 68°F and 77°F (20°C and 25°C); excursions permitted from 59°F to 86°F (15°C to 30°C) [See USP Controlled Room Temperature]. Store in a dry place away from direct heat or sunlight. Keep out of reach of children.

ANORO ELLIPTA should be stored inside the unopened moisture-protective foil tray and only removed from the tray immediately before initial use. Discard ANORO ELLIPTA 6 weeks after opening the foil tray or when the counter reads “0” (after all blisters have been used), whichever comes first. The inhaler is not reusable. Do not attempt to take the inhaler apart.

17 PATIENT COUNSELING INFORMATION

Advise the patient to read the FDA-approved patient labeling (Patient Information and Instructions for Use).

Serious Asthma-Related Events

ANORO ELLIPTA is not indicated for the treatment of asthma. Inform patients that LABAs, such as vilanterol (one of the active ingredients in ANORO ELLIPTA), when used alone (without ICS) for asthma increase the risk of asthma-related hospitalization or asthma-related death. [See Warnings and Precautions (5.1).]

Not for Acute Symptoms

Inform patients that ANORO ELLIPTA is not meant to relieve acute symptoms of COPD and extra doses should not be used for that purpose. Advise patients to treat acute symptoms with an inhaled, short-acting beta2-agonist such as albuterol. Provide patients with such medication and instruct them in how it should be used.

Instruct patients to seek medical attention immediately if they experience any of the following:

- Decreasing effectiveness of inhaled, short-acting beta2-agonists
- Need for more inhalations than usual of inhaled, short-acting beta2-agonists
- Significant decrease in lung function as outlined by the physician

Tell patients they should not stop therapy with ANORO ELLIPTA without physician/provider guidance since symptoms may recur after discontinuation. [See Warnings and Precautions (5.2).]

Do Not Use Additional Long-acting Beta2-agonists

Instruct patients not to use other LABAs for COPD. [See Warnings and Precautions (5.3).]

Paradoxical Bronchospasm

As with other inhaled medicines, ANORO ELLIPTA can cause paradoxical bronchospasm. If paradoxical bronchospasm occurs, instruct patients to discontinue ANORO ELLIPTA and contact their healthcare provider right away. [See Warnings and Precautions (5.5).]

Risks Associated with Beta-agonist Therapy

Inform patients of adverse effects associated with beta2-agonists, such as palpitations, chest pain, rapid heart rate, tremor, or nervousness. Instruct patients to consult a healthcare practitioner immediately should any of these signs and symptoms develop. [See Warnings and Precautions (5.7).]

Worsening of Narrow-Angle Glaucoma

Instruct patients to be alert for signs and symptoms of acute narrow-angle glaucoma (e.g., eye pain or discomfort, blurred vision, visual halos or colored images in association with red eyes from conjunctival congestion and corneal edema). Instruct patients to consult a physician immediately if any of these signs or symptoms develop. [See Warnings and Precautions (5.9).]

Worsening of Urinary Retention

Instruct patients to be alert for signs and symptoms of urinary retention (e.g., difficulty passing urine, painful urination). Instruct patients to consult a physician immediately if any of these signs or symptoms develop. [See Warnings and Precautions (5.10).]

Trademarks are owned by or licensed to the GSK group of companies.
ANORO ELLIPTA was developed in collaboration with Innoviva.

GlaxoSmithKline
Durham, NC 27701

©2023 GSK group of companies or its licensor.

ANR:12PI

PATIENT INFORMATION

ANORO ELLIPTA (a-NOR-oh e-LIP-ta)

(umeclidinium and vilanterol inhalation powder)

for oral inhalation use

What is ANORO ELLIPTA?

- ANORO ELLIPTA combines 2 medicines in 1 inhaler, an anticholinergic medicine (umeclidinium) and a long‑acting beta2-adrenergic agonist (LABA) medicine (vilanterol).
  - Anticholinergic medicines such as umeclidinium and LABA medicines such as vilanterol help the muscles around the airways in your lungs stay relaxed to prevent symptoms such as wheezing, cough, chest tightness, and shortness of breath. These symptoms can happen when the muscles around the airways tighten. This makes it hard to breathe.
- ANORO ELLIPTA is not used to relieve sudden breathing problems and will not replace a rescue inhaler.
- ANORO ELLIPTA is a prescription medicine used long term (chronic) to treat people with chronic obstructive pulmonary disease (COPD). COPD is a chronic lung disease that includes chronic bronchitis, emphysema, or both.
- ANORO ELLIPTA is used as 1 inhalation 1 time each day to improve symptoms of COPD for better breathing and to reduce the number of flare-ups (the worsening of your COPD symptoms for several days).
- ANORO ELLIPTA is not for the treatment of asthma. It is not known if ANORO ELLIPTA is safe and effective in people with asthma.

ANORO ELLIPTA should not be used in children.

It is not known if ANORO ELLIPTA is safe and effective in children.

Do not use ANORO ELLIPTA if you:

- have a severe allergy to milk proteins. Ask your healthcare provider if you are not sure.
- are allergic to umeclidinium, vilanterol, or any of the ingredients in ANORO ELLIPTA. See the end of this Patient Information for a complete list of ingredients in ANORO ELLIPTA.
- have asthma.

Before using ANORO ELLIPTA, tell your healthcare provider about all of your medical conditions, including if you:

- have heart problems.
- have high blood pressure.
- have seizures.
- have thyroid problems.
- have diabetes.
- have liver problems.
- have eye problems such as glaucoma. ANORO ELLIPTA may make your glaucoma worse.
- are allergic to milk proteins.
- have prostate or bladder problems, or problems passing urine. ANORO ELLIPTA may make these problems worse.
- are pregnant or plan to become pregnant. It is not known if ANORO ELLIPTA may harm your unborn baby.
- are breastfeeding or plan to breastfeed. It is not known if the medicines in ANORO ELLIPTA pass into your breast milk and if they can harm your baby.

Tell your healthcare provider about all the medicines you take, including prescription and over-the-counter medicines, vitamins, and herbal supplements. ANORO ELLIPTA and certain other medicines may interact with each other. This may cause serious side effects.

Especially tell your healthcare provider if you take:

- anticholinergics (including tiotropium, ipratropium, aclidinium)
- atropine
- other LABAs (including salmeterol, formoterol, arformoterol, olodaterol, and indacaterol)
- antifungal or anti-HIV medicines

Know the medicines you take. Keep a list of them to show your healthcare provider and pharmacist when you get a new medicine.

How should I use ANORO ELLIPTA?

Read the step-by-step instructions for using ANORO ELLIPTA at the end of this Patient Information.

- Do not use ANORO ELLIPTA unless your healthcare provider has taught you how to use the inhaler and you understand how to use it correctly.
- Use ANORO ELLIPTA exactly as your healthcare provider tells you to use it. Do not use ANORO ELLIPTA more often than prescribed.
- Use 1 inhalation of ANORO ELLIPTA 1 time each day. Use ANORO ELLIPTA at the same time each day.
- If you miss a dose of ANORO ELLIPTA, take it as soon as you remember. Do not take more than 1 inhalation per day. Take your next dose at your usual time. Do not take 2 doses at 1 time.
- If you take too much ANORO ELLIPTA, call your healthcare provider or go to the nearest hospital emergency room right away if you have any unusual symptoms, such as worsening shortness of breath, chest pain, increased heart rate, or shakiness.
- Do not use other medicines that contain a LABA or an anticholinergic for any reason. Ask your healthcare provider or pharmacist if any of your other medicines are LABA or anticholinergic medicines.
- Do not stop using ANORO ELLIPTA unless told to do so by your healthcare provider because your symptoms might get worse. Your healthcare provider will change your medicines as needed.
- ANORO ELLIPTA does not relieve sudden symptoms of COPD and you should not take extra doses of ANORO ELLIPTA to relieve these sudden symptoms. Always have a rescue inhaler with you to treat sudden symptoms. If you do not have a rescue inhaler, call your healthcare provider to have one prescribed for you.
- Call your healthcare provider or get medical care right away if:
  - your breathing problems get worse.
  - you need to use your rescue inhaler more often than usual.
  - your rescue inhaler does not work as well to relieve your symptoms.

What are the possible side effects of ANORO ELLIPTA?

ANORO ELLIPTA can cause serious side effects, including:

- serious problems in people with asthma. People with asthma who take LABA medicines, such as vilanterol (one of the medicines in ANORO ELLIPTA), without also using a medicine called an inhaled corticosteroid, have an increased risk of serious problems from asthma, including death.
  - Call your healthcare provider if breathing problems worsen over time while using ANORO ELLIPTA. You may need a different treatment.
  - Get emergency medical care if:
    - your breathing problems worsen quickly.
    - you use your rescue inhaler medicine, but it does not relieve your breathing problems.
- COPD symptoms that get worse over time. If your COPD symptoms worsen over time, do not increase your dose of ANORO ELLIPTA; instead call your healthcare provider.
- symptoms of using too much of a LABA medicine, including:

- chest pain
- fast or irregular heartbeat
- tremor

- increased blood pressure
- headache
- nervousness

- sudden breathing problems immediately after inhaling your medicine. If you have sudden breathing problems immediately after inhaling your medicine, stop using ANORO ELLIPTA and call your healthcare provider right away.
- serious allergic reactions. Call your healthcare provider or get emergency medical care if you get any of the following symptoms of a serious allergic reaction:

- rash
- hives

- swelling of your face, mouth, and tongue
- breathing problems

- effects on heart.

- increased blood pressure
- a fast or irregular heartbeat, awareness of heartbeat

- chest pain

- effects on nervous system.

- tremor

- nervousness

- new or worsening eye problems including acute narrow-angle glaucoma. You should have regular eye exams while using ANORO ELLIPTA. Acute narrow-angle glaucoma can cause permanent loss of vision if not treated. Symptoms of acute narrow-angle glaucoma may include:

- eye pain or discomfort
- blurred vision
- red eyes

- nausea or vomiting
- seeing halos or bright colors around lights

If you have these symptoms, call your healthcare provider right away before taking another dose.
2. urinary retention. People who take ANORO ELLIPTA may develop new or worse urinary retention. Symptoms of urinary retention may include:

- difficulty urinating
- urinating frequently

- painful urination
- urination in a weak stream or drips

If you have these symptoms of urinary retention, stop taking ANORO ELLIPTA and call your healthcare provider right away before taking another dose.
2. changes in laboratory blood values, including high levels of blood sugar (hyperglycemia) and low levels of potassium (hypokalemia).

Common side effects of ANORO ELLIPTA include:

- sore throat
- common cold symptoms
- pain in your arms or legs
- chest pain

- sinus infection
- constipation
- muscle spasms

- lower respiratory infection
- diarrhea
- neck pain

These are not all the possible side effects of ANORO ELLIPTA.

Call your doctor for medical advice about side effects. You may report side effects to FDA at 1-800-FDA-1088.

How should I store ANORO ELLIPTA?

- Store ANORO ELLIPTA at room temperature between 68°F and 77°F (20°C and 25°C). Keep in a dry place away from heat and sunlight.
- Store ANORO ELLIPTA in the unopened tray and only open when ready for use.
- Safely throw away ANORO ELLIPTA in the trash 6 weeks after you open the tray or when the counter reads “0”, whichever comes first. Write the date you open the tray on the label on the inhaler.
- Keep ANORO ELLIPTA and all medicines out of the reach of children.

General information about the safe and effective use of ANORO ELLIPTA.

Medicines are sometimes prescribed for purposes other than those listed in a Patient Information leaflet. Do not use ANORO ELLIPTA for a condition for which it was not prescribed. Do not give ANORO ELLIPTA to other people, even if they have the same symptoms that you have. It may harm them.

You can ask your healthcare provider or pharmacist for information about ANORO ELLIPTA that is written for health professionals.

What are the ingredients in ANORO ELLIPTA?

Active ingredients: umeclidinium, vilanterol

Inactive ingredients: lactose monohydrate (contains milk proteins), magnesium stearate

For more information about ANORO ELLIPTA, call 1-888-825-5249.

Trademarks are owned by or licensed to the GSK group of companies.

ANORO ELLIPTA was developed in collaboration with Innoviva.

GlaxoSmithKline, Durham, NC 27701

©2022 GSK group of companies or its licensor.

ANR:10PIL

This Patient Information has been approved by the U.S. Food and Drug Administration Revised: October 2022

INSTRUCTIONS FOR USE

INSTRUCTIONS FOR USE

ANORO ELLIPTA (a-NOR-oh e-LIP-ta)

(umeclidinium and vilanterol inhalation powder)

for oral inhalation use

Read this before you start:

- If you open and close the cover without inhaling the medicine, you will lose the dose.
- The lost dose will be securely held inside the inhaler, but it will no longer be available to be inhaled.
- It is not possible to accidentally take a double dose or an extra dose in 1 inhalation.

Your ANORO ELLIPTA inhaler

How to use your inhaler

- ANORO ELLIPTA comes in a tray.
- Peel back the lid to open the tray. See Figure A.
- The tray contains a desiccant to reduce moisture. Do not eat or inhale. Throw it away in the household trash out of reach of children and pets. See Figure B.

Figure A

Figure B

Important Notes:

- Your inhaler contains 30 doses (7 doses if you have a sample or institutional pack).
- Each time you fully open the cover of the inhaler (you will hear a clicking sound), a dose is ready to be inhaled. This is shown by a decrease in the number on the counter.
- If you open and close the cover without inhaling the medicine, you will lose the dose. The lost dose will be held in the inhaler, but it will no longer be available to be inhaled. It is not possible to accidentally take a double dose or an extra dose in 1 inhalation.
- Do not open the cover of the inhaler until you are ready to use it. To avoid wasting doses after the inhaler is ready, do not close the cover until after you have inhaled the medicine.
- Write the “Tray opened” and “Discard” dates on the inhaler label. The “Discard” date is 6 weeks from the date you open the tray.

Check the counter. See Figure C.

Figure C

- Before the inhaler is used for the first time, the counter should show the number 30 (7 if you have a sample or institutional pack). This is the number of doses in the inhaler.
- Each time you open the cover, you prepare 1 dose of medicine.
- The counter counts down by 1 each time you open the cover.

Prepare your dose:

Wait to open the cover until you are ready to take your dose.

Figure D

Step 1. Open the cover of the inhaler. See Figure D.

- Slide the cover down to expose the mouthpiece. You should hear a “click.” The counter will count down by 1 number. You do not need to shake this kind of inhaler. Your inhaler is now ready to use.
- If the counter does not count down as you hear the click, the inhaler will not deliver the medicine. Call your healthcare provider or pharmacist if this happens.

Figure E

Step 2. Breathe out. See Figure E.

- While holding the inhaler away from your mouth, breathe out (exhale) fully. Do not breathe out into the mouthpiece.

Figure F

Step 3. Inhale your medicine. See Figure F.

- Put the mouthpiece between your lips, and close your lips firmly around it. Your lips should fit over the curved shape of the mouthpiece.
- Take 1 long, steady, deep breath in through your mouth. Do not breathe in through your nose.

Figure G

- Do not block the air vent with your fingers. See Figure G.

Figure H

- Remove the inhaler from your mouth and hold your breath for about 3 to 4 seconds (or as long as comfortable for you). See Figure H.

Figure I

Step 4. Breathe out slowly and gently. See Figure I.

- You may not taste or feel the medicine, even when you are using the inhaler correctly.
- Do not take another dose from the inhaler even if you do not feel or taste the medicine.

Figure J

Step 5. Close the inhaler. See Figure J.

- You can clean the mouthpiece if needed, using a dry tissue, before you close the cover. Routine cleaning is not required.
- Slide the cover up and over the mouthpiece as far as it will go.

Important Note: When should you get a refill?

Figure K

- When you have fewer than 10 doses remaining in your inhaler, the left half of the counter shows red as a reminder to get a refill. See Figure K.
- After you have inhaled the last dose, the counter will show “0” and will be empty.
- Throw the empty inhaler away in your household trash out of reach of children and pets.

For more information about ANORO ELLIPTA or how to use your inhaler, call 1-888-825-5249.

Trademarks are owned by or licensed to the GSK group of companies.

ANORO ELLIPTA was developed in collaboration with Innoviva.

GlaxoSmithKline, Durham, NC 27701

©2022 GSK group of companies or its licensor.

ANR:6IFU

This Instructions for Use has been approved by the U.S. Food and Drug Administration Revised: October 2022

PACKAGE LABEL

PRINCIPAL DISPLAY PANEL

NDC 0173-0869-10

ANORO ELLIPTA

(umeclidinium and vilanterol inhalation powder)

62.5 mcg/25 mcg

Rx Only

FOR ORAL INHALATION ONLY

Each blister on one strip contains 62.5 mcg of umeclidinium, magnesium stearate, and lactose monohydrate. Each blister on the other strip contains 25 mcg of vilanterol, magnesium stearate, and lactose monohydrate.

1 ELLIPTA Inhaler containing 30 doses (60 blisters total)

GSK

©2023 GSK group of companies or its licensor.

62000000084535 Rev.1/23